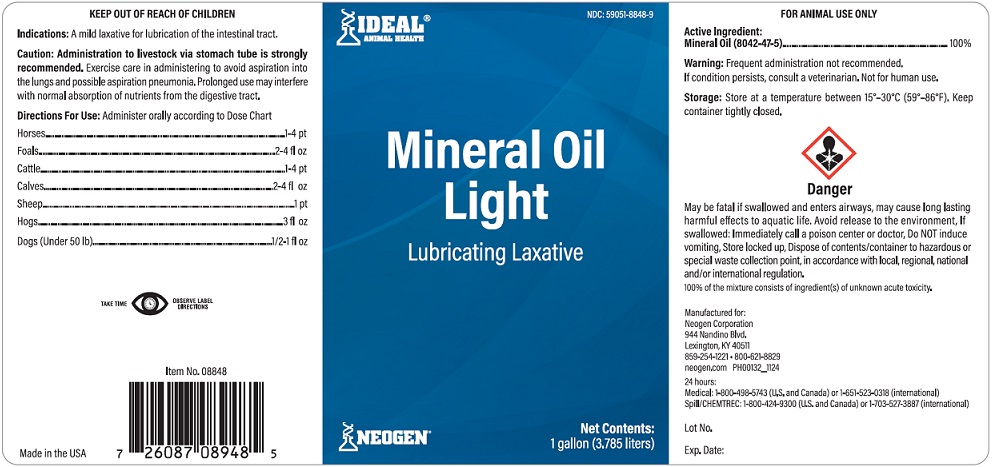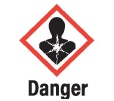 DRUG LABEL: Mineral Oil
NDC: 59051-8848 | Form: OIL
Manufacturer: Neogen Corp
Category: animal | Type: OTC ANIMAL DRUG LABEL
Date: 20251207

ACTIVE INGREDIENTS: Light Mineral Oil 3.785 L/3.785 L

MINERAL OIL LIGHT

FOR ANIMAL USE ONLY

Active Ingredient:

Mineral Oil (8042-47-5) ..................................... 100%

Warning: Frequent administration not recommended.

If condition persists, consult a veterinarian. Not for human use.

Storage: Store at a temperature between 15⁰-30⁰C (59⁰-86⁰F). Keep container tightly closed.

KEEP OUT OF REACH OF CHILDREN

Indications: A mild laxative for lubrication of the intestinal tract.

Caution: Administration to livestock via stomach tube is strongly recommended. Exercise care in administering to avoid aspiration into the lungs and possible aspiration pneumonia. Prolonged use may interfere with normal absorption of nutrients from the digestive tract.

Directions For Use: Administer orally according to Dose Chart:

Horses......................................................1-4 pt
Foals.........................................................2-4 fl oz
Cattle.........................................................1-4 pt
Calves.......................................................2-4 fl oz
Sheep...........................................................1 pt
Hogs............................................................3 fl oz
Dogs (Under 50 lb)................................1/2-1 fl oz

May be fatal if swallowed and enters airways, may cause long lasting harmful effects to aquatic life. Avoid release to the environment, If swallowed: Immediately call a poison center or doctor, Do NOT induce vomiting, Store locked up, Dispose of contents/container to hazardous or special waste collection point, in accordance with local, regional, national and/or international regulation.

100% of the mixture consists of ingredient(s) of unknown acute toxicity.

Manufactured for:

Neogen Corporation

944 Nandino Blvd,

Lexington, KY 40511

859-254-1221 · 800-621-8829

Neogen.com PH00132_1124

24hours:

Medical: 1-800-498-5743 (U.S. and Canada) or 1-651-523-0318 (international)

Spill/CHEMTREC: 1-800-424-9300 (U.S. and Canada) or 1-703-527-3887 (international)

Made in the USA